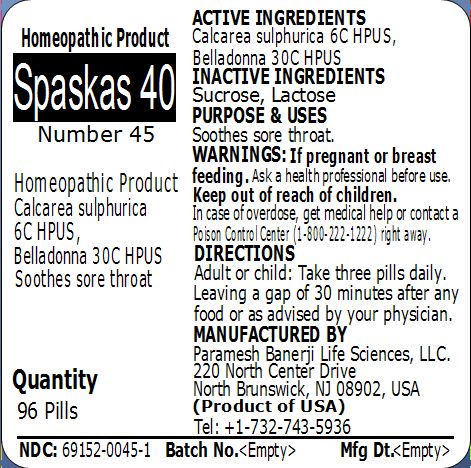 DRUG LABEL: Spaskas 40 (Number 45)
NDC: 69152-0045 | Form: PELLET
Manufacturer: Paramesh Banerji Life Sciences LLC
Category: homeopathic | Type: HUMAN OTC DRUG LABEL
Date: 20150228

ACTIVE INGREDIENTS: ATROPA BELLADONNA 30 [hp_C]/1 1; CALCIUM SULFATE ANHYDROUS 6 [hp_C]/1 1
INACTIVE INGREDIENTS: SUCROSE; LACTOSE

Active Ingredients

Calcarea sulphurica 6C HPUS, Belladonna 30C HPUS

Inactive Ingredients

Sucrose, Lactose

Purpose

Soothes sore throat

Uses

Soothes sore throat

Warnings

If pregnant or breast feeding ask a health professional before use.

Keep out of reach of children. In case of overdose, get medical help or contact a Poison Control Center (1-800-222-1222) right away.

Direction

Adult or child: Take three pills daily. Leaving a gap of 30 minutes after any food or as advised by your physician.

Manufactured by

Paramesh Banerji Life Sciences, LLC

220 North Center Drive

North Brunswick, NJ 08902, USA

Product of USA

Tel: +1-732-743-5936

Principal Display Panel

Homeopathic Product

Spaskas 40

Number 45

Homeopathic Product

Calcarea sulphurica 6C HPUS, Belladonna 30C HPUS

Soothes sore throat

Quantity

96 Pills